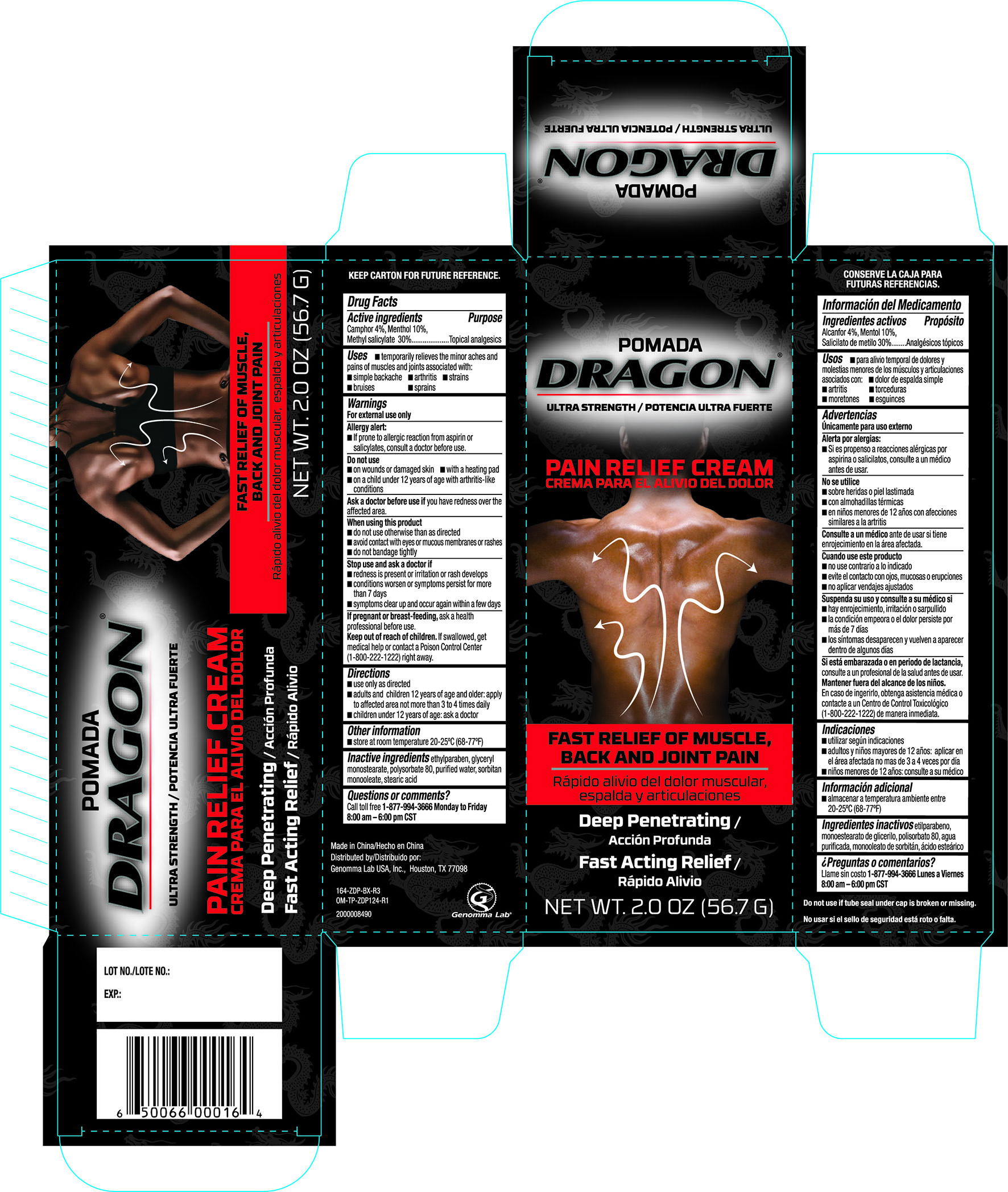 DRUG LABEL: POMADA DRAGON PAIN RELIEVING
NDC: 55038-001 | Form: CREAM
Manufacturer: TELEVISA CONSUMER PRODUCTS USA
Category: otc | Type: HUMAN OTC DRUG LABEL
Date: 20251017

ACTIVE INGREDIENTS: CAMPHOR (SYNTHETIC) 40 mg/1 g; MENTHOL 100 mg/1 g; METHYL SALICYLATE 300 mg/1 g
INACTIVE INGREDIENTS: GLYCERYL MONOSTEARATE; ETHYLPARABEN; POLYSORBATE 80; WATER; SORBITAN MONOOLEATE; STEARIC ACID

Pomada Dragon Pain Relieving Muscle Rub Cream 2oz 164

Active ingredients Purpose

Camphor 4%.................................................................................Topical analgesic

Menthol 10%.................................................................................Topical analgesic

Methyl Salicylate 30%.....................................................................Topical analgesic

Uses

Temporarily relieves the minor aches and pains of muscles and joints associated with:

- simple backache
- arthritis
- strains
- bruises
- sprains

Warnings

For external use only

Allergy alert

- if prone to allergic reaction from aspirin or salicylates, consult a doctor before use.

Do not use

- on wounds or damaged skin
- with a heating pad
- on a child under 12years of age with arthritis-like conditions

Ask a doctor before use

if you have redness over the affected area

When using this product

- do not use otherwise than as directed
- avoid contact with eyes or mucous membranes or rashes
- do not bandage tightly

Stop use and ask a doctor if

- redness is present or irritation or rash develops
- conditions worsen or symptoms persist for more than 7 days
- symptoms clear up and occur again within a few days

PREGNANCY OR BREAST FEEDING

If pregnant or breast-feeding, ask a health professional before use.

Keep out of reach of children to avoid accidental ingestion.

If swallowed, get medical help or contact a Poison Control Center immediately.

Directions

- use only as directed
- adults and children 12 years of age and older: apply to affected area not more than 3 to 4 times daily
- children under 12 years of age: ask a doctor

Other information

- Store between 20o and 25o C (68o and 77oF)

INACTIVE INGREDIENT

Inactive ingredients: ethylparaben, glyceryl monostearate, polysorbate 80, purified water, sorbitan monooleate, stearic acid

DOSAGE AND ADMINISTRATION

Distributed By:

Genomma Lab USA, Inc.

Houston, TX 77027

Made in China